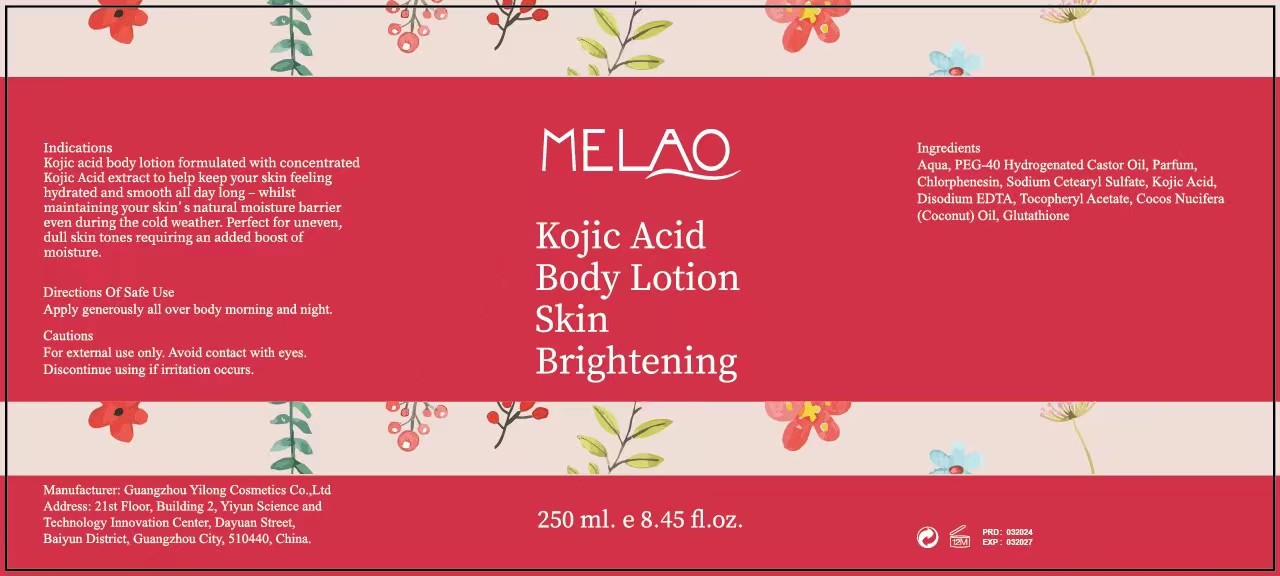 DRUG LABEL: MELAO Kojic Acid BodyLotion
NDC: 74458-357 | Form: LOTION
Manufacturer: Guangzhou Yilong Cosmetics Co., Ltd
Category: otc | Type: HUMAN OTC DRUG LABEL
Date: 20241016

ACTIVE INGREDIENTS: KOJIC ACID 0.5 g/100 mL; GLUTATHIONE 1 g/100 mL
INACTIVE INGREDIENTS: ALPHA-TOCOPHEROL ACETATE; PARFUMIDINE; CHLORPHENESIN; POLYOXYL 40 HYDROGENATED CASTOR OIL; COCONUT OIL; WATER; SODIUM CETOSTEARYL SULFATE; EDETATE DISODIUM

MELAO Kojic Acid Body Lotion

ACTIVE INGREDIENT

Tocopheryl Acetate 0.3% Kojic Acid 0.5 Glutathione 1%

INACTIVE INGREDIENT

Aqua

PEG-40 Hydrogenated Castor Oil

Parfum

Chlorphenesin

Sodium Cetearyl Sulfate

Disodium EDTA

Cocos Nucifera (Coconut) Oil

PURPOSE

Brightens skin tone.

WARNINGS

For external use only.

INDICATIONS AND USAGE

Apply generously all over body moring and night.

Stop use and ask a doctor if rash occurs.

Do not use on damaged or broken skin.

When using this product keep out of eyes. Rinse with water to remove.

Keep out of reach of children. If swallowed, get medical help or contact a Poison Control Center right away.

DOSAGE AND ADMINISTRATION

Apply generously all over body moring and night.